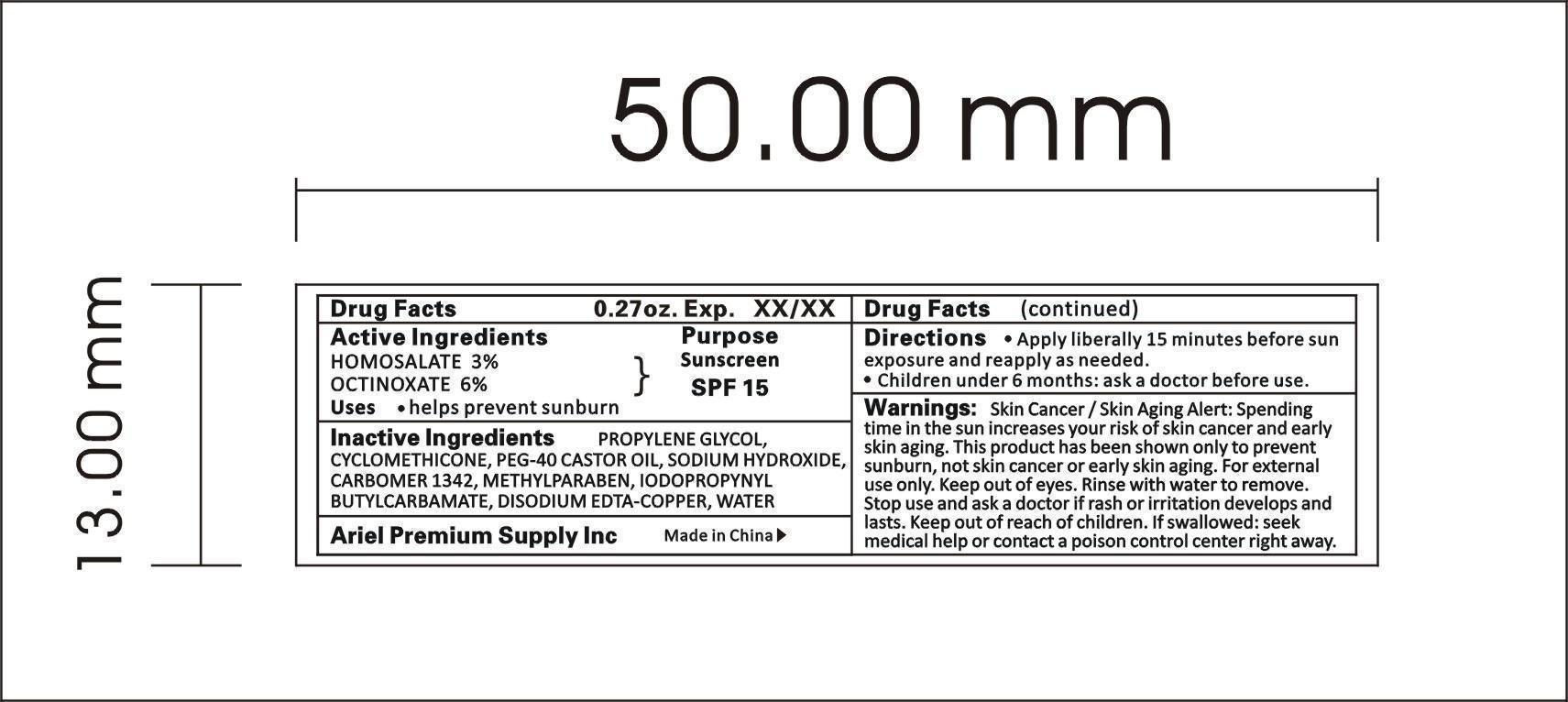 DRUG LABEL: SUN BLOCK SPRARY
NDC: 47993-215 | Form: SPRAY
Manufacturer: NINGBO JIANGBEI OCEAN STAR TRADING CO.,LTD
Category: otc | Type: HUMAN OTC DRUG LABEL
Date: 20150215

ACTIVE INGREDIENTS: Homosalate 3 g/100 g; OCTINOXATE 6 g/100 g
INACTIVE INGREDIENTS: CYCLOMETHICONE 6 g/100 g; PEG-40 CASTOR OIL 1 g/100 g; DISODIUM EDTA-COPPER 0.03 g/100 g; CARBOMER 1342 0.2 g/100 g; Propylene Glycol 8 g/100 g; SODIUM HYDROXIDE 0.5 g/100 g; IODOPROPYNYL BUTYLCARBAMATE 0.07 g/100 g; METHYLPARABEN 0.15 g/100 g; WATER 75.05 g/100 g

Active Ingredients

Active ingredients--------------purpose

Ethyl Alcohol 62%------------antiseptic

Uses:
Reduces bacteria on the skin. Recommended for repeated use.

Warnings:

For external use only.Flammable:Keep away from heat for flame.Do no use in or near the eyes. In case of contact, rinse eyes thoroughly with water.

Directions:

Place enough product in your palm to thoroughly cover your hands. Rub hands together briskly until dry.

Other Information

Do not store above 110F(43C) May discolor certain fabric or surfaces. Harmful to wood finishes and plastics.

KEEP OUT OF REACH OF CHILDREN

Children under 6 years of age should be super vised when using this product.

Inactive Ingredients:

Water,Glycerin,Isopropyl Myristate, Propylene Glycol,Tocopheryl Acetate, Aminomethyl Propanol, Carbomer, Fragrance